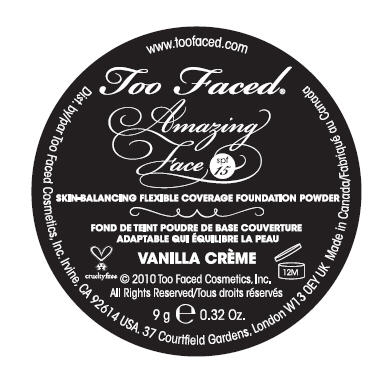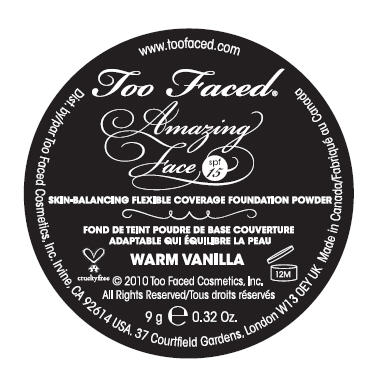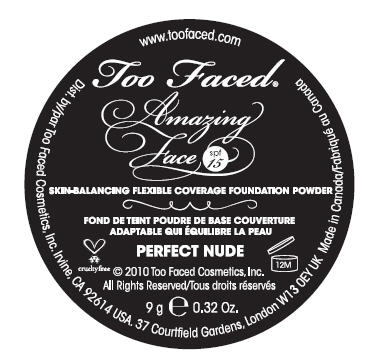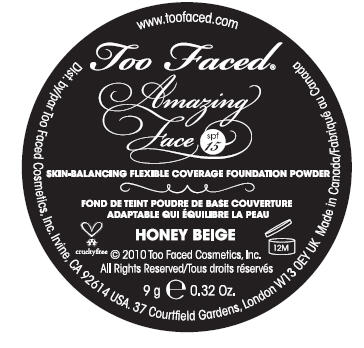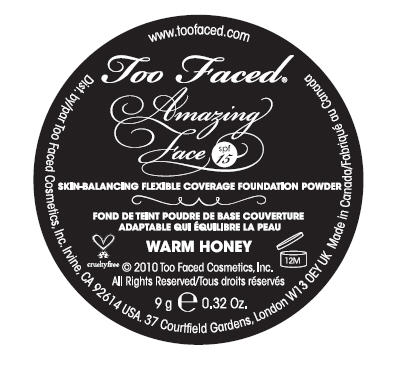 DRUG LABEL: Amazing Face 
NDC: 66559-1471 | Form: POWDER
Manufacturer: Cosmetica Laboratories Inc.
Category: otc | Type: HUMAN OTC DRUG LABEL
Date: 20100511

ACTIVE INGREDIENTS: Octisalate 0.27 g/9 g; Octinoxate 0.45 g/9 g

Amazing
Face
spf
15

uses

helps protect against sunburn.

warnings

for external use only.

when using this product keep out of eyes. rinse with water to remove.

stop use and ask doctor if rash or irritation develops and lasts.

keep out of reach of children.

active ingredients

Octinoxate (5.0%), Octisalate (3.0%).

inactive ingredients

Talc, Silica, Dimethicone, Serenoa Serrulata Fruit Extract, Argania Spinosa Kernel Extract, Sesamum Indicum (Sesame) Seed Extract, Bambusa Arundinacea Stem Powder, Octyldodecly Stearate, Octyldodecyl Stearoyl Stearate, Caprylyl Glycol, Phenoxyethanol. (+/-): Titanium Dioxide (CI 77891), Iron Oxides (CI 77491 , CI 77492, CI 77499).

Dist. by/Distr. par Too Faced Cosmetics, Inc. Irvine, CA 92614 USA
37 Courtfield Gardens, London W13 OEY UK Made in Canada
©2010 Too Faced Cosmetics, Inc. All Rights Reserved
www.toofaced.com

PRINCIPAL DISPLAY PANEL - 9 g Lid Label

Too Faced®

Amazing
Face

spf
15

SKIN-BALANCING FLEXIBLE COVERAGE FOUNDATION POWDER

VANILLA CRÈME

crueltyfree

© 2010 Too Faced Cosmetics, Inc.
All Rights Reserved/

9 g e 0.32 Oz.

PRINCIPAL DISPLAY PANEL - 9 g Lid Label

Too Faced®

Amazing
Face

spf
15

SKIN-BALANCING FLEXIBLE COVERAGE FOUNDATION POWDER

PERFECT NUDE

crueltyfree

© 2010 Too Faced Cosmetics, Inc.
All Rights Reserved/

9 g e 0.32 Oz.

PRINCIPAL DISPLAY PANEL - 9 g Lid Label

Too Faced®

Amazing
Face

spf
15

SKIN-BALANCING FLEXIBLE COVERAGE FOUNDATION POWDER

HONEY BEIGE

crueltyfree

© 2010 Too Faced Cosmetics, Inc.
All Rights Reserved/

9 g e 0.32 Oz.

PRINCIPAL DISPLAY PANEL - 9 g Lid Label

Too Faced®

Amazing
Face

spf
15

SKIN-BALANCING FLEXIBLE COVERAGE FOUNDATION POWDER

WARM HONEY

crueltyfree

© 2010 Too Faced Cosmetics, Inc.
All Rights Reserved/

9 g e 0.32 Oz.

PRINCIPAL DISPLAY PANEL - 9 g Lid Label

Too Faced®

Amazing
Face

spf
15

SKIN-BALANCING FLEXIBLE COVERAGE FOUNDATION POWDER

WARM VANILLA

crueltyfree

© 2010 Too Faced Cosmetics, Inc.
All Rights Reserved/

9 g e 0.32 Oz.